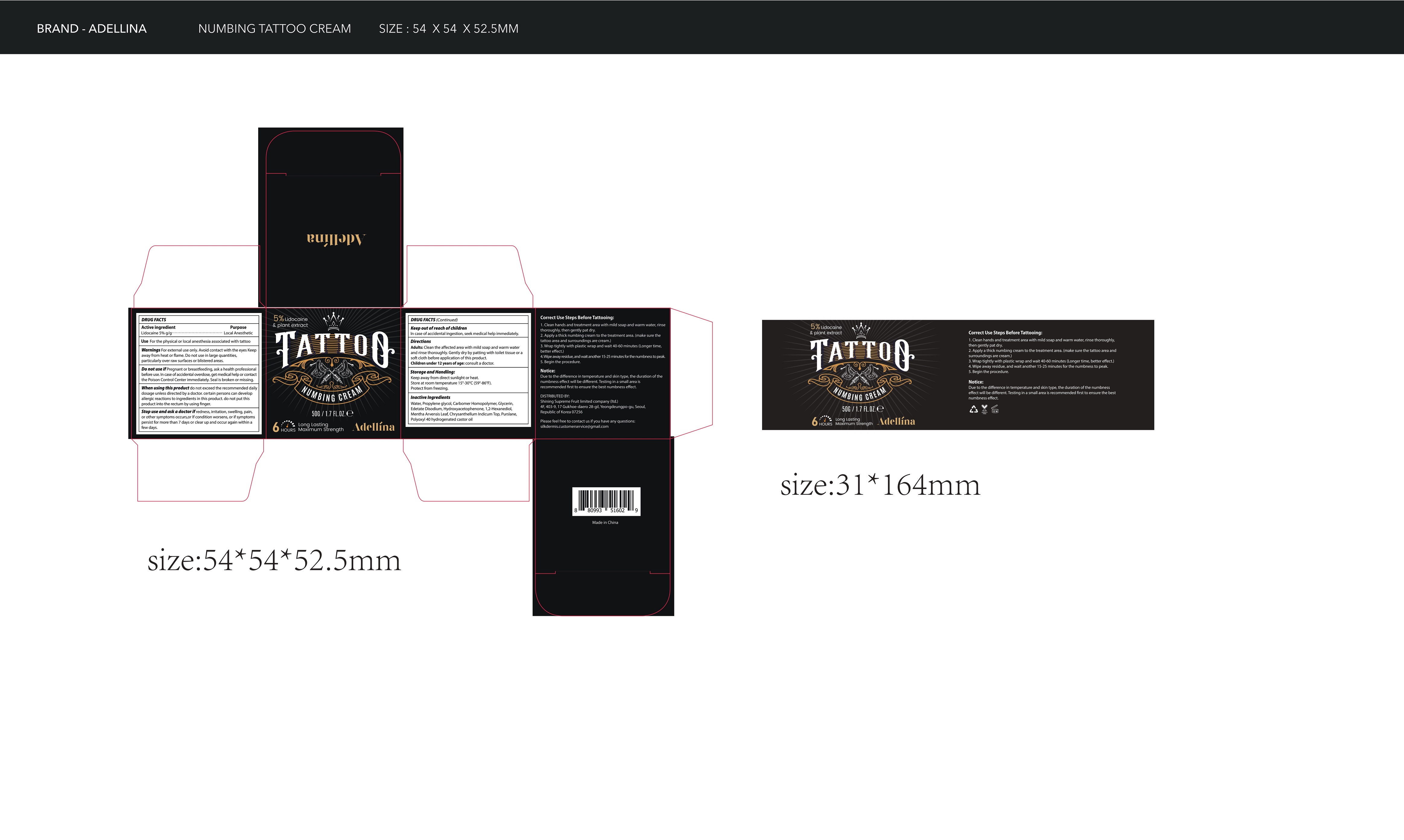 DRUG LABEL: Adellina TATTOO NUMBING
NDC: 83596-001 | Form: CREAM
Manufacturer: Aramode
Category: otc | Type: HUMAN OTC DRUG LABEL
Date: 20231115

ACTIVE INGREDIENTS: LIDOCAINE 5 g/100 g
INACTIVE INGREDIENTS: WATER; PROPYLENE GLYCOL; CARBOMER HOMOPOLYMER, UNSPECIFIED TYPE; GLYCERIN; EDETATE DISODIUM; HYDROXYACETOPHENONE; 1,2-HEXANEDIOL; MENTHA ARVENSIS LEAF; CHRYSANTHELLUM INDICUM TOP; PURSLANE; POLYOXYL 40 HYDROGENATED CASTOR OIL

Active Ingredient(s)

Lidocaine 5% g/g. Purpose: Local Anesthetic

Purpose

Local Anesthetic

Use

For the physical or local anesthesia associated with tattoo

Warnings

For external use only.Avoid contact with the eyes Keepaway from heat or flame. Do not use in large quantities,particularly over raw surfaces or blistered areas.

- Do not use if Pregnant or breastfeeding, ask a health professionalbefore use.In case of accidental overdose, get medical help or contactthe Poison Control Center immediately. Seal is broken or missing.

When using this product do not exceed the recommended dailydosage unless directed by a doctor. certain persons can developallergic reactions to ingredients in this product. do not put thisproduct into the rectum by using finger.

Stop use and ask a doctor if redness, irritation, swelling, pain,or other symptoms occurs,or lf condition worsens, or if symptomspersist for more than 7 days or clear up and occur again within afew days.

Keep out of reach of children

In case of accidental ingestion, seek medical help immediately.

Directions

Adults: Clean the affected area with mild soap and warm waterand rinse thoroughly.Gently dry by patting with toilet tissue or asoft cloth before application of this product.
Children under 12 years of age: consult a doctor.

Storage and Handling:

- Keep away from direct sunlight or heat.
  Store at room temperature 15°-30℃(59-86°F).
- Protect from freezing.

Inactive ingredients

AQUA, Propylene glycol, Carbomer, Glycerin, Disodium edta,Hydroxyacetophenone,1,2-Hexanediol, Mentha Arvensis LeafExtract, Chrysanthellum Indicum Extract, Portulaca OleraceaExtract, PEG-40 hydrogenated castor oil

Package Label - Principal Display Panel

50g NDC: 83596-001-01